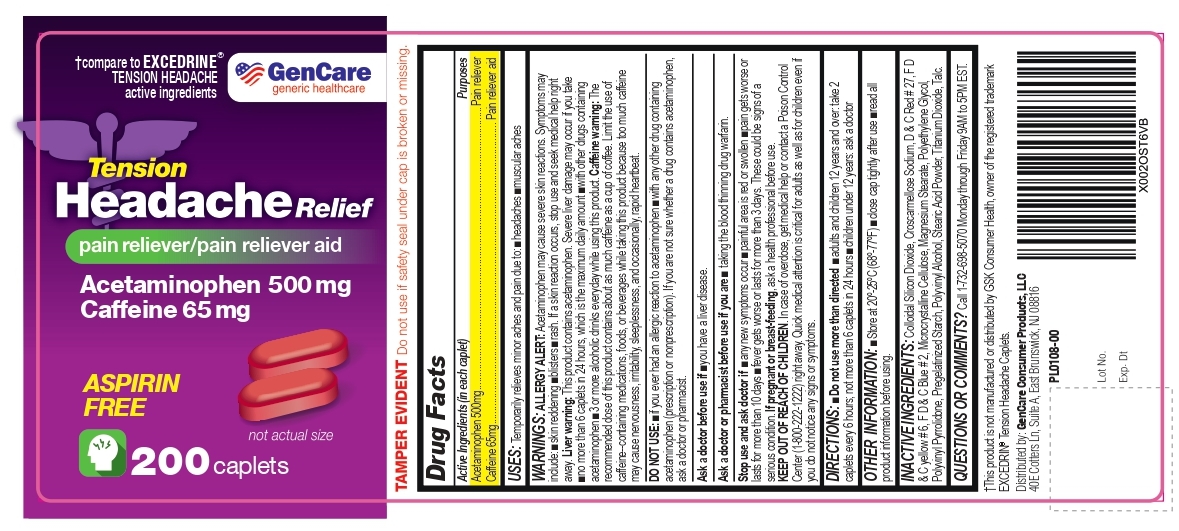 DRUG LABEL: Tension Headache Relief
NDC: 72090-004 | Form: TABLET
Manufacturer: Pioneer Life Sciences, LLC
Category: otc | Type: HUMAN OTC DRUG LABEL
Date: 20251229

ACTIVE INGREDIENTS: ACETAMINOPHEN 500 mg/1 1; CAFFEINE 65 mg/1 1
INACTIVE INGREDIENTS: CROSCARMELLOSE SODIUM; POLYETHYLENE GLYCOL, UNSPECIFIED; POLYVINYL ALCOHOL, UNSPECIFIED; TALC; MICROCRYSTALLINE CELLULOSE; SILICON DIOXIDE; STARCH, CORN; TITANIUM DIOXIDE; D&C RED NO. 27; FD&C BLUE NO. 2; MAGNESIUM STEARATE; STEARIC ACID; FD&C YELLOW NO. 6

Tension Headache Relief (Acetaminophen 500mg and caffeine 65mg)

Active Ingredients (in each caplet)

Acetaminophen 500mg
Caffeine 65 mg

Purpose

Acetaminophen 500mg............................................................................................................Pain reliever
Caffeine 65mg................................................................................................................... Pain reliever aid

Uses:

temporarily relieves minor aches and pains due to:

•headache
•muscular aches

Warnings:

Allergy alert:Acetaminophen may cause severe skin reactions. Symptoms may include:

•skin reddening
•blisters
•rash

If a skin reaction occurs, stop use and seek medical help right away.

Liver warning:This product contains acetaminophen. Severe liver damage may occur if you take

•more than 6 caplets in 24 hours, which is the maximum daily amount
•with other drugs containing acetaminophen
•3 or more alcoholic drinks every day while using this product

Caffeine warning:The recommended dose of this product contains about as much caffeine as a cup of coffee. Limit the use of caffeine-containing medications, foods, or beverages while taking this product because too much caffeine may cause nervousness, irritability, sleeplessness, and occasionally, rapid heartbeat.

Do not use

•if you are allergic to acetaminophen
•with any other drug containing acetaminophen (prescription or nonprescription). If you are not sure whether a drug contains acetaminophen, ask a doctor or pharmacist.

Ask Doctor:

Ask a doctor before use if

•you have liver disease

ASK DOCTOR/PHARMACIST:

Ask a doctor or pharmacist before use if you are

•taking the blood thinning drug warfarin

Stop use and ask doctor if

■any new symptoms occur

■painful area is red or swollen

■pain gets worse or lasts for more than 10 days

■fever gets worse or lasts for more than 3 days. These could be signs of a serious condition.

PREGNANCY

If pregnant or breast-feeding, ask a health professional before use.

KEEP OUT OF REACH OF CHILDREN

In case of overdose, get medical help or contact a Poison Control Center (1-800-222-1222) right away. Quick medical attention is critical for adults as well as for children even if you do not notice any signs or symptoms.

DIRECTIONS

• Do not use more than directed

■adults and children 12 years and over: take 2 caplets every 6 hours; not more than 6 caplets in 24 hours

■chlidren under 12 years: ask a doctor

OTHER INFORMATION

•store at 20°-25°C (68°-77°F)

•close cap tightly after use
•read all product information before using.

INACTIVE INGREDIENTS

Colloidal Silicon Dioxide, Croscarmellose Sodium, D & C Red # 27, F D & C yellow # 6, F D & C Blue # 2, Microcrystalline Cellulose, Magnesium Stearate, Polyethylene Glycol, Polyvinyl Pyrrolidone, Pregelatinized Starch, Polyvinyl Alcohol, Stearic Acid Powder, Titanium Dioxide, Talc.

QUESTIONS OR COMMENTS?

Call 1-732-698-5070 Monday through Friday 9AM to 5PM EST.